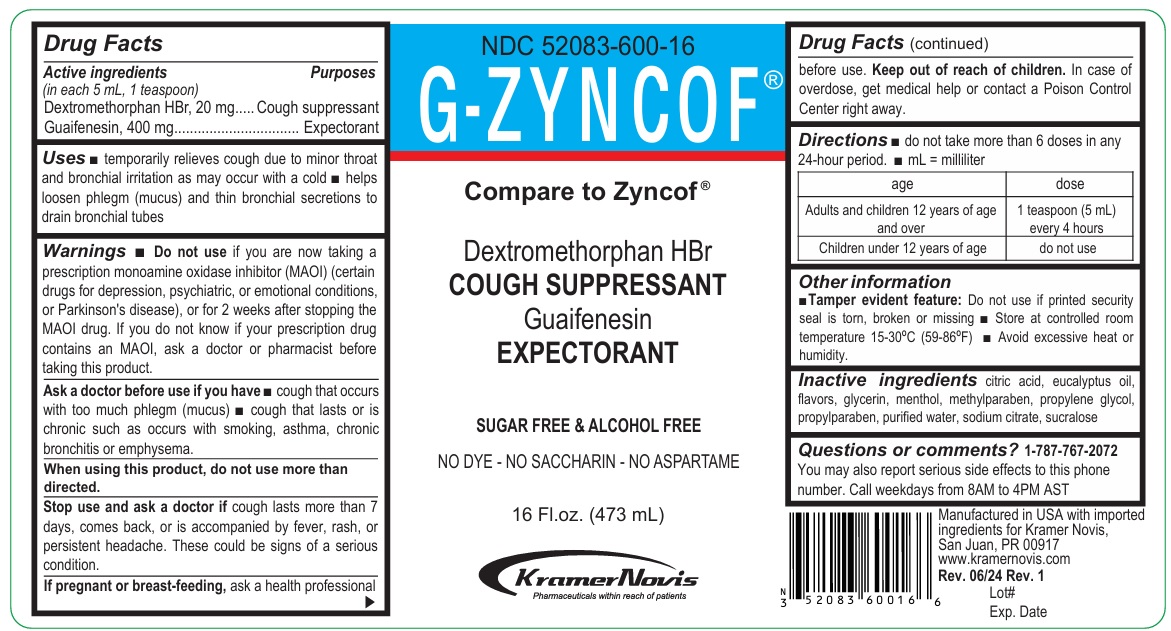 DRUG LABEL: G-ZYNCOF
NDC: 52083-600 | Form: SYRUP
Manufacturer: Kramer Novis
Category: otc | Type: HUMAN OTC DRUG LABEL
Date: 20251114

ACTIVE INGREDIENTS: DEXTROMETHORPHAN HYDROBROMIDE 20 mg/5 mL; GUAIFENESIN 400 mg/5 mL
INACTIVE INGREDIENTS: CITRIC ACID MONOHYDRATE; EUCALYPTUS OIL; GLYCERIN; MENTHOL, UNSPECIFIED FORM; METHYLPARABEN; PROPYLENE GLYCOL; PROPYLPARABEN; WATER; SODIUM CITRATE, UNSPECIFIED FORM; SUCRALOSE

G-ZYNCOF

Active ingredients (in each 5 mL, 1 teaspoon)

Dextromethorphan HBr, 20 mg
Guaifenesin, 400 mg

Purposes

Cough suppressant
Expectorant

Uses

• temporarily relieves cough due to minor throat and bronchial irritation as may occur with a cold • helps loosen phlegm (mucus) and thin bronchial secretions to drain bronchial tubes

Warnings

• Do not use if you are now taking a prescription monoamine oxidase inhibitor (MAOI) (certain drugs for depression, psychiatric or emotional conditions, or Parkinson’s disease), or for 2 weeks after stopping the MAOI drug. If you do not know if your prescription drug contains an MAOI, ask a doctor or pharmacist before taking this product.

Ask a doctor before use if you have • cough that occurs with too much phlegm (mucus) • cough that lasts or is chronic such as occurs with smoking, asthma, chronic bronchitis, or emphysema.

When using this product, do not use more than directed.

Stop use and ask a doctor if cough lasts more than 7 days, comes back, or is accompanied by fever, rash, or persistent headache. These could be signs of a serious condition.

If pregnant or breast-feeding, ask a health professional before use.

Keep out of reach of children. In case of overdose, get medical help or contact a Poison Control Center right away.

Directions

• do not take more than 6 doses in any 24-hour period. • mL = milliliter

age | dose
Adults and children 12 years of age and over | 1 teaspoon (5 mL) every 4 hours
Children under 12 years of age | do not use

Other information

• Tamper evident feature: Do not use if printed security seal is torn, broken or missing • Store at controlled room temperature 15-30°C (59-86°F) • Avoid excessive heat or humidity.

Inactive ingredients

citric acid, eucalyptus oil, flavors, glycerin, menthol, methylparaben, propylene glycol, propylparaben, purified water, sodium citrate, sucralose

Questions or comments?

1-787-767-2072
You may also report serious side effects to this phone number. Call weekdays from 8AM to 4PM AST

Dextromethorphan HBr
COUGH SUPPRESSANT

Guaifenesin
EXPECTORANT

SUGAR FREE & ALCOHOL FREE

NO DYE - NO SACCHARIN - NO ASPARTAME

KramerNovis
Pharmaceuticals within reach of patients

Manufactured in USA with imported ingredients for Kramer Novis, San Juan, PR 00917

www.kramernovis.com

Directions: (The following changes were made)

• mL=milliliter
• A table was included with the dosage instructions according to age:

age | dose
Adults and children 12 years of age and over | 1 teaspoon (5 mL) every 4 hours
Children under 12 years of age | do not use